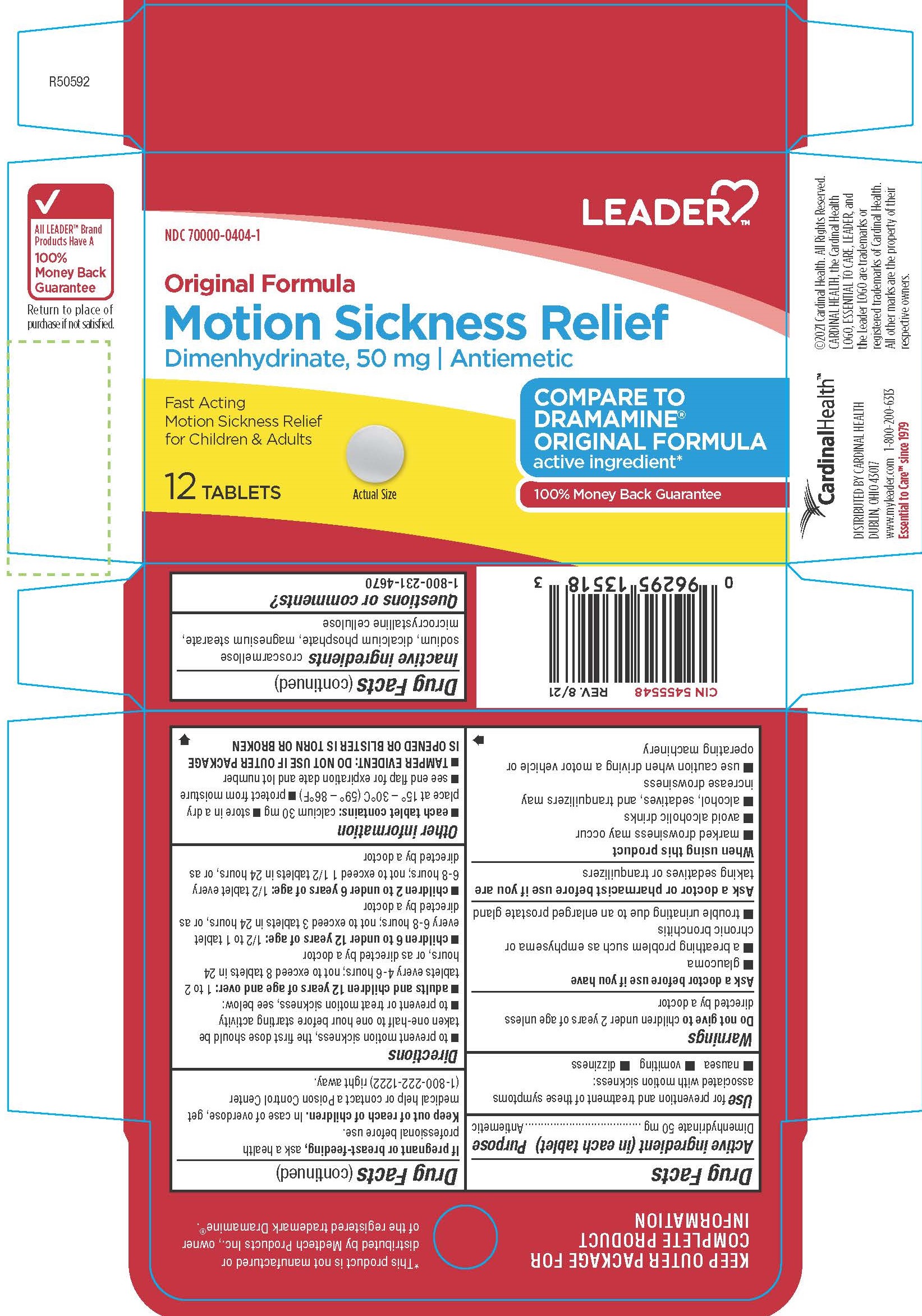 DRUG LABEL: Dimenhydrinate
NDC: 70000-0404 | Form: TABLET
Manufacturer: LEADER/ Cardinal Health 110, Inc.
Category: otc | Type: HUMAN OTC DRUG LABEL
Date: 20260220

ACTIVE INGREDIENTS: DIMENHYDRINATE 50 mg/1 1
INACTIVE INGREDIENTS: CROSCARMELLOSE SODIUM; MAGNESIUM STEARATE; DIBASIC CALCIUM PHOSPHATE DIHYDRATE; MICROCRYSTALLINE CELLULOSE

1006-Cardinal

Drug Facts

Active ingredient (in each tablet)

Dimenhydrinate 50 mg

Purpose

Antiemetic

Uses

for the prevention and treatment of nausea, vomiting, or dizziness associated with motion sickness

WARNINGS

Do not give to children under 2 years of age unless directed by a doctor

Ask a doctor before use if you have

■ glaucoma

■ a breathing problem such as emphysema or chronic bronchitis

■ trouble urinating due to an enlarged prostate gland

Ask a doctor or pharmacist before use if you are taking sedatives or tranquilizers

When using this product

■ marked drowsiness may occur

■ avoid alcoholic drinks

■ alcohol, sedatives, and tranquilizers may increase drowsiness

■ use caution when driving a motor vehicle or operating machinery

PREGNANCY OR BREAST FEEDING

If pregnant or breast-feeding, ask a health professional before use.

Keep out of reach of children.

OVERDOSAGE

In case of overdose, get medical help or contact a Poison Control Center (1-800-222-1222) right away.

Directions

■ to prevent motion sickness, the first dose should be taken one-half to one hour before starting activity

■ adults and children 12 years of age and over: 1 to 2 tablets every 4-6 hours; not to exceed 8 tablets in 24 hours, or as directed by a doctor

■ children 6 to under 12 years of age: 1/2 to 1 tablet every 6-8 hours; not to exceed 3 tablets in 24 hours, or as directed by a doctor

■ children 2 to under 6 years of age: 1/2 tablet every 6-8 hours; not to exceed 1 1/2 tablets in 24 hours, or as directed by a doctor

Other information

■ each tablet contains: calcium 30 mg

■ store in a dry place at 15° – 30°C (59° – 86°F)

■ protect from moisture
■ see end flap for expiration date and lot number
■ TAMPER EVIDENT: DO NOT USE IF OUTER PACKAGE IS OPENED OR BLISTER IS TORN OR BROKEN

INACTIVE INGREDIENT

croscarmellose sodium, dicalcium phosphate, magnesium stearate, microcrystalline cellulose

Questions or comments?

1-800-231-4670

*This product is not manufactured or distributed by Medtech Products Inc., owner of the registered trademark Dramamine®

KEEP OUTER PACKAGE FOR COMPLETE PRODUCT INFORMATION

©2021 Cardinal Health. All Rights Reserved.

CARDINAL HEALTH, the Cardinal Health LOGO, LEADER, and the Leader LOGO are trademarks or registered trademarks of Cardinal Health. All other marks are the property of their respective owners

DISTRIBUTED BY CARDINAL HEALTH

DUBLIN, OHIO 43017

www.myleader.com 1-800-200-6313

Essential to Care™ since 1979

All LEADER™ Brand

Products Have A

100%

Money Back

Guarantee

PACKAGE LABEL

LEADER

NDC 7000-0404-1

Original Formula

Motion Sickness Relief

Dimenhydrinate, 50 mg/ Antiemetic

COMPARE TO DRAMAMINE® ORIGINAL FORMULA active ingredient*

Fast Acting Motion Sickness Relief for Children & Adults

12 Tablets